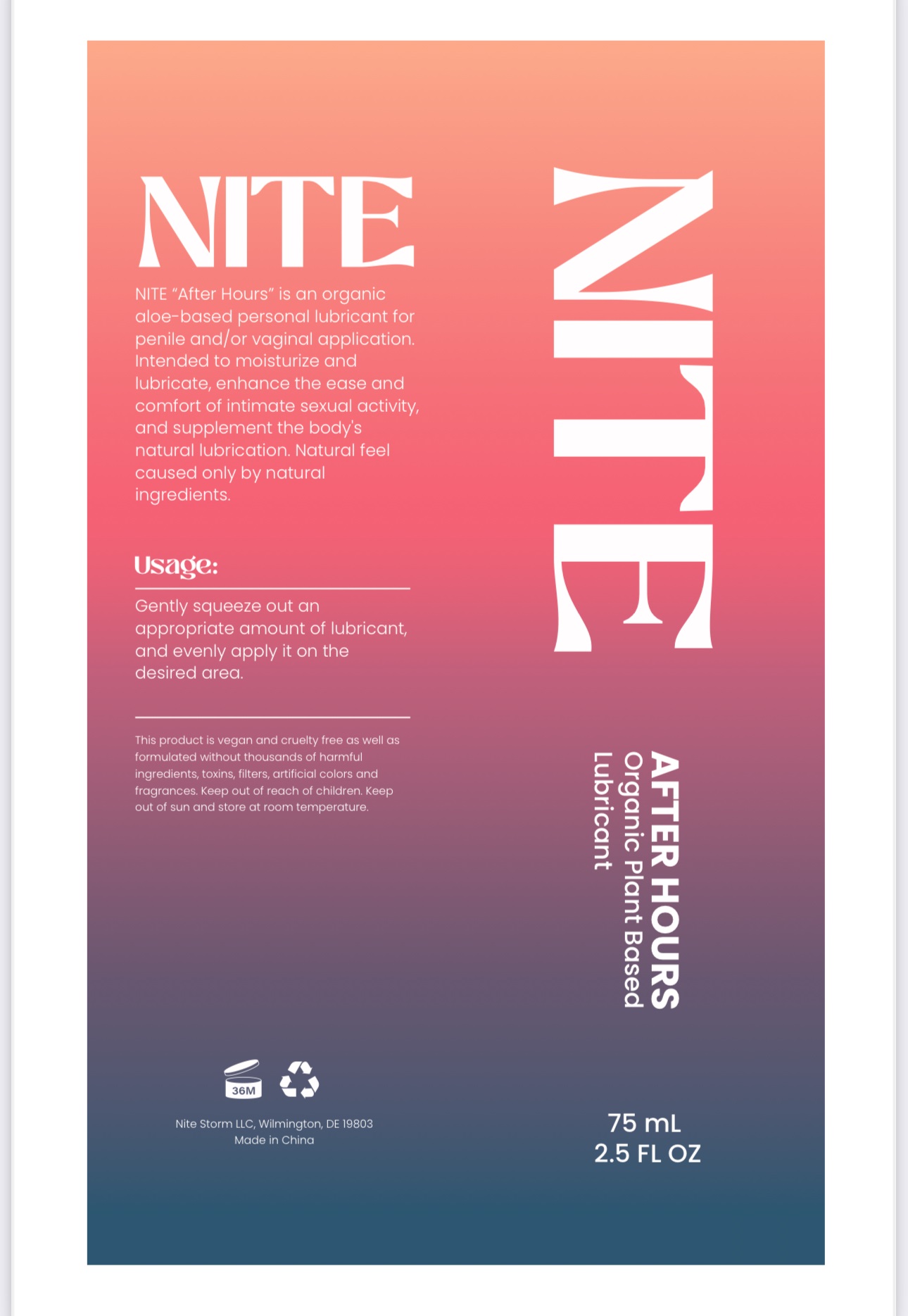 DRUG LABEL: Nite
NDC: 85094-708 | Form: OIL
Manufacturer: Nite Storm LLC
Category: otc | Type: HUMAN OTC DRUG LABEL
Date: 20250101

ACTIVE INGREDIENTS: HYDROXYETHYL CELLULOSE (140 CPS AT 5%) 0.38 g/75 mL
INACTIVE INGREDIENTS: GLYCERIN; WATER

Usage:

Gently squeeze out an appropriate amount of lubricant, and evenly apply it on the desired area.

Description

NITE "After Hours" is an organic aloe-based personal lubricant for penile and /or vaginal application. Intended to moisturize and lubricate, enhance the ease and comform of initimate secual activity, and supplement the body's natural lubrication. Natural feel caused only by natural ingredients.

Warning:

If irritaiton or discomfort occurs, discontinue use immediately and consult a physician.

Keep out of eyes and ears.

Keep out of reach of Children and pets.

Very slippery, clean spills immediately.

This product is not a contraceptive or spermicide.

Bottle may leak if not stored upright.

Store at ambient weather.

Keep out of reach of children and pets

Dosage & Administration

Apply a small amount to genital areas. Reapply as needed or desired.

Stop Use

If irritation or discomfort occurs, discontinue the use and consult a physician. Very slippery on surfaces, clean spills immediately.

Ask doctor

If irritation or discomfort occurs, discontinue the use and consult a physician

Purpose:

NITE "After Hours" is an organic aloe-based personal lubricant for penile and/or vaginal appliation. Intended to moisturize and lubricate, enhance the ease and comfort of initimate secual activity.

Inactive Ingredient:

HYDROXYETHYL CELLULOSE

Active Ingredient

HYDROXYETHYL CELLULOSE